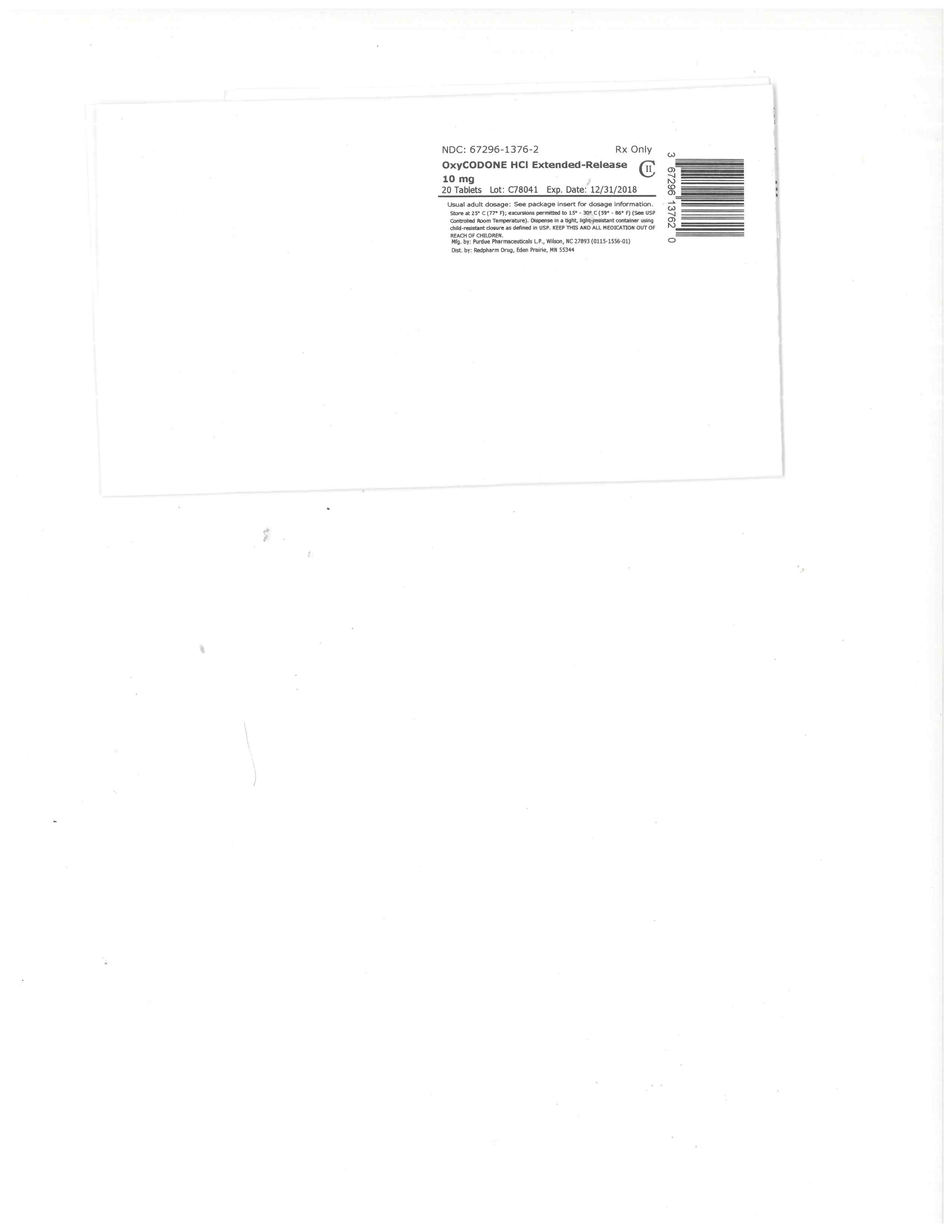 DRUG LABEL: OXYCODONE HYDROCHLORIDE
NDC: 67296-1376 | Form: TABLET, FILM COATED, EXTENDED RELEASE
Manufacturer: RedPharm Drug, Inc.
Category: prescription | Type: HUMAN PRESCRIPTION DRUG LABEL
Date: 20220121
DEA Schedule: CII

ACTIVE INGREDIENTS: OXYCODONE HYDROCHLORIDE 10 mg/1 1
INACTIVE INGREDIENTS: BUTYLATED HYDROXYTOLUENE; POLYETHYLENE GLYCOL, UNSPECIFIED; MAGNESIUM STEARATE; TITANIUM DIOXIDE; POLYETHYLENE GLYCOL 400; HYPROMELLOSES; HYDROXYPROPYL CELLULOSE (1600000 WAMW)

BOXED WARNING

WARNING: ADDICTION, ABUSE AND MISUSE; LIFE-THREATENING RESPIRATORY DEPRESSION; ACCIDENTAL INGESTION; NEONATAL OPIOID WITHDRAWAL SYNDROME; AND CYTOCHROME P450 3A4 INTERACTION

Addiction, Abuse, and Misuse

OXYCODONE HCl EXTENDED-RELEASE TABLETS expose patients and other users to the risks of opioid addiction, abuse and misuse, which can lead to overdose and death. Assess each patient’s risk prior to prescribing OXYCODONE HCl EXTENDED-RELEASE TABLETS and monitor all patients regularly for the development of these behaviors or conditions [see Warnings and Precautions (5.1)].

Life-Threatening Respiratory Depression

Serious, life-threatening, or fatal respiratory depression may occur with use of OXYCODONE HCl EXTENDED-RELEASE TABLETS. Monitor for respiratory depression, especially during initiation of OXYCODONE HCl EXTENDED-RELEASE TABLETS or following a dose increase. Instruct patients to swallow OXYCODONE HCl EXTENDED-RELEASE TABLETS whole; crushing, chewing, or dissolving OXYCODONE HCl EXTENDED-RELEASE TABLETS can cause rapid release and absorption of a potentially fatal dose of oxycodone [see Warnings and Precautions (5.2)].

Accidental Ingestion

Accidental ingestion of even one dose of OXYCODONE HCl EXTENDED-RELEASE TABLETS, especially by children, can result in a fatal overdose of oxycodone [see Warnings and Precautions (5.2)].

Neonatal Opioid Withdrawal Syndrome

Prolonged use of OXYCODONE HCl EXTENDED-RELEASE TABLETS during pregnancy can result in neonatal opioid withdrawal syndrome, which may be life-threatening if not recognized and treated, and requires management according to protocols developed by neonatology experts. If opioid use is required for a prolonged period in a pregnant woman, advise the patient of the risk of neonatal opioid withdrawal syndrome and ensure that appropriate treatment will be available [see Warnings and Precautions (5.3)].

Cytochrome P450 3A4 Interaction

The concomitant use of OXYCODONE HCl EXTENDED-RELEASE TABLETS with all cytochrome P450 3A4 inhibitors may result in an increase in oxycodone plasma concentrations, which could increase or prolong adverse drug effects and may cause potentially fatal respiratory depression. In addition, discontinuation of a concomitantly used cytochrome P450 3A4 inducer may result in an increase in oxycodone plasma concentration. Monitor patients receiving OXYCODONE HCl EXTENDED-RELEASE TABLETS and any CYP3A4 inhibitor or inducer [see Warnings and Precautions (5.14) and Clinical Pharmacology (12.3)].

HIGHLIGHTS OF PRESCRIBING INFORMATION

These highlights do not include all the information needed to use OXYCODONE HCl EXTENDED-RELEASE TABLETS safely and effectively. See full prescribing information for OXYCODONE HCl EXTENDED-RELEASE TABLETS.
OXYCODONE HCL EXTENDED-RELEASE TABLETS, for oral use, CII
Initial U.S. Approval: 1950

WARNING: ADDICTION, ABUSE AND MISUSE; LIFE-THREATENING RESPIRATORY DEPRESSION; ACCIDENTAL INGESTION; NEONATAL OPIOID WITHDRAWAL SYNDROME; AND CYTOCHROME P450 3A4 INTERACTION
SEE FULL PRESCRIBING INFORMATION FOR COMPLETE BOXED WARNING.

OXYCODONE HCl EXTENDED-RELEASE TABLETS expose users to risks of addictions, abuse and misuse, which can lead to overdose and death. Assess each patient's risk before prescribing and monitor regularly for development of these behaviors and conditions. (5.1)
Serious, life-threatening, or fatal respiratory depression may occur. Monitor closely, especially upon initiation or following a dose increase. Instruct patients to swallow OXYCODONE HCl EXTENDED-RELEASE TABLETS whole to avoid exposure to a potentially fatal dose of oxycodone. (5.2)
Accidental ingestion of OXYCODONE HCl EXTENDED-RELEASE TABLETS, especially in children, can result in a fatal overdose of oxycodone. (5.2)
Prolonged use of OXYCODONE HCl EXTENDED-RELEASE TABLETS during pregnancy can result in neonatal opioid withdrawal syndrome, which may be life-threatening if not recognized and treated. If opioid use is required for a prolonged period in a pregnant woman, advise the patient of the risk of neonatal opioid withdrawal syndrome and ensure that appropriate treatment will be available. (5.3)
Initiation of CYP3A4 inhibitors (or discontinuation of CYP3A4 inducers) can result in a fatal overdose of oxycodone from OXYCODONE HCl EXTENDED-RELEASE TABLETS. (5.14, 12.3)

FULL PRESCRIBING INFORMATION: CONTENTS*

WARNING: ADDICTION, ABUSE AND MISUSE; LIFE-THREATENING RESPIRATORY DEPRESSION; ACCIDENTAL INGESTION; NEONATAL OPIOID WITHDRAWAL SYNDROME; AND CYTOCHROME P450 3A4 INTERACTION
1 INDICATIONS AND USAGE
2 DOSAGE AND ADMINISTRATION
2.1 Important Dosage and Administration Instructions
2.2 Initial Dosage in Adults who are not Opioid-Tolerant
2.3 Conversion from Opioids to OXYCODONE HCl EXTENDED-RELEASE TABLETS in Adults
2.4 Initial Dosage in Pediatric Patients 11 Years and Older
2.5 Titration and Maintenance of Therapy in Adults and Pediatric Patients 11 Years and Older
2.6 Dosage Modifications with Concomitant Use of Central Nervous System Depressants
2.7 Dosage Modifications in Geriatric Patients who are Debilitated and not Opioid-Tolerant
2.8 Dosage Modifications in Patients with Hepatic Impairment
2.9 Discontinuation of OXYCODONE HCl EXTENDED-RELEASE TABLETS
3 DOSAGE FORMS AND STRENGTHS
4 CONTRAINDICATIONS
5 WARNINGS AND PRECAUTIONS
5.1 Addiction, Abuse, and Misuse
5.2 Life-Threatening Respiratory Depression
5.3 Neonatal Opioid Withdrawal Syndrome
5.4 Interactions with Central Nervous System Depressants
5.5 Use in Elderly, Cachectic, and Debilitated Patients
5.6 Use in Patients with Chronic Pulmonary Disease
5.7 Hypotensive Effects
5.8 Use in Patients with Head Injury or Increased Intracranial Pressure
5.9 Difficulty in Swallowing and Risk for Obstruction in Patients at Risk for a Small Gastrointestinal Lumen
5.10 Use in Patients with Gastrointestinal Conditions
5.11 Use in Patients with Convulsive or Seizure Disorders
5.12 Avoidance of Withdrawal
5.13 Driving and Operating Machinery
5.14 Cytochrome P450 3A4 Inhibitors and Inducers
5.15 Laboratory Monitoring
6 ADVERSE REACTIONS
6.1 Clinical Trial Experience
6.2 Postmarketing Experience
7 DRUG INTERACTIONS
7.1 CNS Depressants
7.2 Drugs Affecting Cytochrome P450 Isoenzymes
7.3 Mixed Agonist/Antagonist and Partial Agonists Opioid Analgesics
7.4 Muscle Relaxants
7.5 Diuretics
7.6 Anticholinergics
8 USE IN SPECIFIC POPULATIONS
8.1 Pregnancy
8.2 Labor and Delivery
8.3 Nursing Mothers
8.4 Pediatric Use
8.5 Geriatric Use
8.6 Hepatic Impairment
8.7 Renal Impairment
8.8 Gender Differences
9 DRUG ABUSE AND DEPENDENCE
9.1 Controlled Substance
9.2 Abuse
9.3 Dependence
10 OVERDOSAGE
11 DESCRIPTION
12 CLINICAL PHARMACOLOGY
12.1 Mechanism of Action
12.2 Pharmacodynamics
12.3 Pharmacokinetics
13 NONCLINICAL TOXICOLOGY
13.1 Carcinogenesis, Mutagenesis, Impairment of Fertility
14 CLINICAL STUDIES
16 HOW SUPPLIED/STORAGE AND HANDLING
17 PATIENT COUNSELING INFORMATION

*
Sections or subsections omitted from the full prescribing information are not listed.

1 INDICATIONS AND USAGE

OXYCODONE HCl EXTENDED-RELEASE TABLETS are indicated for the management of pain severe enough to require daily, around-the-clock, long-term opioid treatment and for which alternative treatment options are inadequate in:

Adults; and
Opioid-tolerant pediatric patients 11 years of age and older who are already receiving and tolerate a minimum daily opioid dose of at least 20 mg oxycodone orally or its equivalent.

Limitations of Use

Because of the risks of addiction, abuse, and misuse with opioids, even at recommended doses, and because of the greater risks of overdose and death with extended-release opioid formulations [see Warnings and Precautions (5.1)], reserve OXYCODONE HCl EXTENDED-RELEASE TABLETS for use in patients for whom alternative treatment options (e.g., non-opioid analgesics or immediate-release opioids) are ineffective, not tolerated, or would be otherwise inadequate to provide sufficient management of pain.
OXYCODONE HCl EXTENDED-RELEASE TABLETS are not indicated as an as-needed (prn) analgesic.

2 DOSAGE AND ADMINISTRATION

2.1 Important Dosage and Administration Instructions

OXYCODONE HCl EXTENDED-RELEASE TABLETS should be prescribed only by healthcare professionals who are knowledgeable in the use of potent opioids for the management of chronic pain.

Initiate the dosing regimen for each patient individually, taking into account the patient's prior analgesic treatment experience, and risk factors for addiction, abuse, and misuse [see Warnings and Precautions (5.1)].
Monitor patients closely for respiratory depression, especially within the first 24-72 hours of initiating OXYCODONE HCl EXTENDED-RELEASE TABLETS therapy [see Warnings and Precautions (5.2)].
Must take OXYCODONE HCl EXTENDED-RELEASE TABLETS whole, with enough water to ensure complete swallowing immediately after placing in the mouth. Must take OXYCODONE HCl EXTENDED-RELEASE TABLETS one tablet at a time and must not pre-soak, lick or otherwise wet the tablet prior to placing in the mouth [see Warnings and Precautions (5.9)].Cutting, breaking, crushing, chewing, or dissolving OXYCODONE HCl EXTENDED-RELEASE TABLETS will result in uncontrolled delivery of oxycodone and can lead to overdose or death [see Warnings and Precautions (5.1)].

OXYCODONE HCl EXTENDED-RELEASE TABLETS 60 mg and 80 mg tablets, a single dose greater than 40 mg, or a total daily dose greater than 80 mg are only for use in patients in whom tolerance to an opioid of comparable potency has been established.

2.2 Initial Dosage in Adults who are not Opioid-Tolerant

The starting dosage for patients who are not opioid tolerant is OXYCODONE HCl EXTENDED-RELEASE TABLETS 10 mg orally every 12 hours. Adult patients who are opioid tolerant are those receiving, for one week or longer, at least 60 mg oral morphine per day, 25 mcg transdermal fentanyl per hour, 30 mg oral oxycodone per day, 8 mg oral hydromorphone per day, 25 mg oral oxymorphone per day, or an equianalgesic dose of another opioid.

Use of higher starting doses in patients who are not opioid tolerant may cause fatal respiratory depression [see Warnings and Precautions (5.2)].

2.3 Conversion from Opioids to OXYCODONE HCl EXTENDED-RELEASE TABLETS in Adults

Conversion from Other Oral Oxycodone Formulations to OXYCODONE HCl EXTENDED-RELEASE TABLETS

If switching from other oral oxycodone formulations to OXYCODONE HCl EXTENDED-RELEASE TABLETS, administer one half of the patient's total daily oral oxycodone dose as OXYCODONE HCl EXTENDED-RELEASE TABLETS every 12 hours.

Conversion from Other Opioids to OXYCODONE HCl EXTENDED-RELEASE TABLETS

There are no established conversion ratios for conversion from other opioids to OXYCODONE HCl EXTENDED-RELEASE TABLETS defined by clinical trials. Discontinue all other around-the-clock opioid drugs when OXYCODONE HCl EXTENDED-RELEASE TABLETS therapy is initiated and initiate dosing using OXYCODONE HCl EXTENDED-RELEASE TABLETS 10 mg orally every 12 hours.

It is safer to underestimate a patient’s 24-hour oral oxycodone requirements and provide rescue medication (e.g., immediate-release opioid) than to overestimate the 24-hour oral oxycodone requirements which could result in adverse reactions. While useful tables of opioid equivalents are readily available, there is substantial inter-patient variability in the relative potency of different opioids.

Conversion from Methadone to OXYCODONE HCl EXTENDED-RELEASE TABLETS

Close monitoring is of particular importance when converting from methadone to other opioid agonists. The ratio between methadone and other opioid agonists may vary widely as a function of previous dose exposure. Methadone has a long half-life and can accumulate in the plasma.

Conversion from Transdermal Fentanyl to OXYCODONE HCl EXTENDED-RELEASE TABLETS

If switching from transdermal fentanyl patch to OXYCODONE HCl EXTENDED-RELEASE TABLETS, ensure that the patch has been removed for at least 18 hours prior to starting OXYCODONE HCI EXTENDED-RELEASE TABLETS. Although there has been no systematic assessment of such conversion, start with a conservative conversion: substitute 10 mg of OXYCODONE HCI EXTENDED-RELEASE TABLETS every 12 hours for each 25 mcg per hour fentanyl transdermal patch. Follow the patient closely during conversion from transdermal fentanyl to OXYCODONE HCl EXTENDED-RELEASE TABLETS, as there is limited documented experience with this conversion.

2.4 Initial Dosage in Pediatric Patients 11 Years and Older

The following dosing information is for use only in pediatric patients 11 years and older already receiving and tolerating opioids for at least five consecutive days. For the two days immediately preceding dosing with OXYCODONE HCl EXTENDED-RELEASE TABLETS, patients must be taking a minimum of 20 mg per day of oxycodone or its equivalent. OXYCODONE HCl EXTENDED-RELEASE TABLETS is not appropriate for use in pediatric patients requiring less than a 20 mg total daily dose. Table 1, based on clinical trial experience, displays the conversion factor when switching pediatric patients 11 years and older (under the conditions described above) from opioids to OXYCODONE HCl EXTENDED-RELEASE TABLETS.

Discontinue all other around-the-clock opioid drugs when OXYCODONE HCl EXTENDED-RELEASE TABLETS therapy is initiated.

Although tables of oral and parenteral equivalents are readily available, there is substantial inter-patient variability in the relative potency of different opioid drugs and formulations. As such, it is preferable to underestimate a patient’s 24-hour oral oxycodone requirements and provide rescue medication (e.g., immediate-release opioid) than to overestimate the 24-hour oral oxycodone requirements and manage an adverse reaction.

Consider the following when using the information in Table 1.

This is not a table of equianalgesic doses.

The conversion factors in this table are only for the conversion from one of the listed oral opioid analgesics to OXYCODONE HCl EXTENDED-RELEASE TABLETS.

The table cannot be used to convert from OXYCODONE HCl EXTENDED-RELEASE TABLETS to another opioid. Doing so will result in an over-estimation of the dose of the new opioid and may result in fatal overdose.

The formula for conversion from prior opioids, including oral oxycodone, to the daily dose of OXYCODONE HCl EXTENDED-RELEASE TABLETS is mg per day of prior opioid x factor = mg per day of OXYCODONE HCl EXTENDED-RELEASE TABLETS. Divide the calculated total daily dose by 2 to get the every-12-hour OXYCODONE HCl EXTENDED-RELEASE TABLETS dose. If rounding is necessary, always round the dose down to the nearest OXYCODONE HCl EXTENDED-RELEASE TABLET strength available.

Table 1: Conversion Factors When Switching Pediatric Patients 11 Years and Older to OXYCODONE HCl EXTENDED-RELEASE TABLETS

*
For patients receiving high-dose parenteral opioids, a more conservative conversion is warranted. For example, for high-dose parenteral morphine, use 1.5 instead of 3 as a multiplication factor.

Prior Opioid Conversion Factor
Oral Parenteral*
Oxycodone 1 -
Hydrocodone 0.9 -
Hydromorphone 4 20
Morphine 0.5 3
Tramadol 0.17 0.2

Step #1: To calculate the estimated total OXYCODONE HCl EXTENDED-RELEASE TABLETS daily dosage using Table 1:

For pediatric patients taking a single opioid, sum the current total daily dosage of the opioid and then multiply the total daily dosage by the approximate conversion factor to calculate the approximate OXYCODONE HCl EXTENDED-RELEASE TABLETS daily dosage.

For pediatric patients on a regimen of more than one opioid, calculate the approximate oxycodone dose for each opioid and sum the totals to obtain the approximate OXYCODONE HCl EXTENDED-RELEASE TABLETS daily dosage.

For pediatric patients on a regimen of fixed-ratio opioid/non-opioid analgesic products, use only the opioid component of these products in the conversion.

Step #2: If rounding is necessary, always round the dosage down to the nearest OXYCODONE HCl EXTENDED-RELEASE TABLET strength available and initiate OXYCODONE HCl EXTENDED-RELEASE TABLETS therapy with that dose. If the calculated OXYCODONE HCl EXTENDED-RELEASE TABLETS total daily dosage is less than 20 mg, there is no safe strength for conversion and do not initiate OXYCODONE HCl EXTENDED-RELEASE TABLETS.

Example conversion from a single opioid (e.g., hydrocodone) to OXYCODONE HCl EXTENDED-RELEASE TABLETS: Using theconversion factor of 0.9 for oral hydrocodone in Table 1, a total daily hydrocodone dosage of 50 mg is converted to 45 mg of oxycodone per day or 22.5 mg of OXYCODONE HCl EXTENDED-RELEASE TABLETS every 12 hours. After rounding down to the nearest strength available, the recommended OXYCODONE HCl EXTENDED-RELEASE TABLETS starting dosage is 20 mg every 12 hours.

Step #3: Close observation and titration are warranted until pain management is stable on the new opioid. Monitor patients for signs and symptoms of opioid withdrawal or for signs of over-sedation/toxicity after converting patients to OXYCODONE HCl EXTENDED-RELEASE TABLETS. [seeDosage and Administration (2.5)] for important instructions on titration and maintenance of therapy.

There is limited experience with conversion from transdermal fentanyl to OXYCODONE HCl EXTENDED-RELEASE TABLETS in pediatric patients 11 years and older. If switching from transdermal fentanyl patch to OXYCODONE HCl EXTENDED-RELEASE TABLETS, ensure that the patch has been removed for at least 18 hours prior to starting OXYCODONE HCl EXTENDED-RELEASE TABLETS. Although there has been no systematic assessment of such conversion, start with a conservative conversion: substitute 10 mg of OXYCODONE HCl EXTENDED-RELEASE TABLETS every 12 hours for each 25 mcg per hour fentanyl transdermal patch. Follow the patient closely during conversion from transdermal fentanyl to OXYCODONE HCl EXTENDED-RELEASE TABLETS.

If using asymmetric dosing, instruct patients to take the higher dose in the morning and the lower dose in the evening.

2.5 Titration and Maintenance of Therapy in Adults and Pediatric Patients 11 Years and Older

Individually titrate OXYCODONE HCl EXTENDED-RELEASE TABLETS to a dosage that provides adequate analgesia and minimizes adverse reactions. Continually reevaluate patients receiving OXYCODONE HCl EXTENDED-RELEASE TABLETS to assess the maintenance of pain control, signs and symptoms of opioid withdrawal, and adverse reactions, as well as monitoring for the development of addiction, abuse and misuse. Frequent communication is important among the prescriber, other members of the healthcare team, the patient, and the caregiver/family during periods of changing analgesic requirements, including initial titration. During chronic therapy, periodically reassess the continued need for the use of opioid analgesics.

Patients who experience breakthrough pain may require a dosage increase of OXYCODONE HCl EXTENDED-RELEASE TABLETS or may need rescue medication with an appropriate dose of an immediate-release analgesic. If the level of pain increases after dose stabilization, attempt to identify the source of increased pain before increasing the OXYCODONE HCl EXTENDED-RELEASE TABLETS dosage. Because steady-state plasma concentrations are approximated in 1 day, OXYCODONE HCl EXTENDED-RELEASE TABLETS dosage may be adjusted every 1 to 2 days. If unacceptable opioid-related adverse reactions are observed, the subsequent dose may be reduced. Adjust the dosage to obtain an appropriate balance between management of pain and opioid-related adverse reactions.

There are no well-controlled clinical studies evaluating the safety and efficacy with dosing more frequently than every 12 hours. As a guideline for pediatric patients 11 years and older, the total daily oxycodone dosage usually can be increased by 25% of the current total daily dosage. As a guideline for adults, the total daily oxycodone dosage usually can be increased by 25% to 50% of the current total daily dosage, each time an increase is clinically indicated.

2.6 Dosage Modifications with Concomitant Use of Central Nervous System Depressants

If the patient is currently taking a central nervous system (CNS) depressant and the decision is made to begin OXYCODONE HCl EXTENDED-RELEASE TABLETS, start with 1/3 to 1/2 the recommended starting dosage of OXYCODONE HCl EXTENDED-RELEASE TABLETS and monitor patients for signs of respiratory depression, sedation, and hypotension [see Warnings and Precautions (5.4), Drug Interactions (7.1)].

2.7 Dosage Modifications in Geriatric Patients who are Debilitated and not Opioid-Tolerant

For geriatric patients who are debilitated and not opioid tolerant, start dosing patients at 1/3 to 1/2 the recommended starting dosage and titrate the dosage cautiously [see Use in Specific Populations (8.5)].

2.8 Dosage Modifications in Patients with Hepatic Impairment

For patients with hepatic impairment, start dosing patients at 1/3 to 1/2 the recommended starting dosage followed by careful dosage titration [see Clinical Pharmacology (12.3)].

2.9 Discontinuation of OXYCODONE HCl EXTENDED-RELEASE TABLETS

When the patient no longer requires therapy with OXYCODONE HCl EXTENDED-RELEASE TABLETS, gradually titrate the dosage downward to prevent signs and symptoms of withdrawal in the physically dependent patient. Do not abruptly discontinue OXYCODONE HCl EXTENDED-RELEASE TABLETS.

3 DOSAGE FORMS AND STRENGTHS

10 mg film-coated extended-release tablets (round, white-colored, bi-convex tablets debossed with OP on one side and 10 on the other)
15 mg film-coated extended-release tablets (round, gray-colored, bi-convex tablets debossed with OP on one side and 15 on the other)
20 mg film-coated extended-release tablets (round, pink-colored, bi-convex tablets debossed with OP on one side and 20 on the other)
30 mg film-coated extended-release tablets (round, brown-colored, bi-convex tablets debossed with OP on one side and 30 on the other)
40 mg film-coated extended-release tablets (round, yellow-colored, bi-convex tablets debossed with OP on one side and 40 on the other)
60 mg film-coated extended-release tablets (round, red-colored, bi-convex tablets debossed with OP on one side and 60 on the other)
80 mg film-coated extended-release tablets (round, green-colored, bi-convex tablets debossed with OP on one side and 80 on the other)

4 CONTRAINDICATIONS

OXYCODONE HCl EXTENDED-RELEASE TABLETS are contraindicated in patients with:

Significant respiratory depression
Acute or severe bronchial asthma in an unmonitored setting or in the absence of resuscitative equipment
Known or suspected paralytic ileus and gastrointestinal obstruction
Hypersensitivity (e.g., anaphylaxis) to oxycodone[seeAdverse Reactions (6.2)]

5 WARNINGS AND PRECAUTIONS

5.1 Addiction, Abuse, and Misuse

OXYCODONE HCl EXTENDED-RELEASE TABLETS contain oxycodone, a Schedule II controlled substance. As an opioid, OXYCODONE HCl EXTENDED-RELEASE TABLETS expose users to the risks of addiction, abuse, and misuse [see Drug Abuse and Dependence (9)]. As modified-release products such as OXYCODONE HCl EXTENDED-RELEASE TABLETS deliver the opioid over an extended period of time, there is a greater risk for overdose and death due to the larger amount of oxycodone present [see Drug Abuse and Dependence (9)].

Although the risk of addiction in any individual is unknown, it can occur in patients appropriately prescribed OXYCODONE HCl EXTENDED-RELEASE TABLETS. Addiction can occur at recommended doses and if the drug is misused or abused.

Assess each patient’s risk for opioid addiction, abuse or misuse prior to prescribing OXYCODONE HCl EXTENDED-RELEASE TABLETS, and monitor all patients receiving OXYCODONE HCl EXTENDED-RELEASE TABLETS for the development of these behaviors or conditions. Risks are increased in patients with a personal or family history of substance abuse (including drug or alcohol abuse or addiction) or mental illness (e.g., major depression). The potential for these risks should not, however, prevent the proper management of pain in any given patient. Patients at increased risk may be prescribed modified-release opioid formulations such as OXYCODONE HCl EXTENDED-RELEASE TABLETS, but use in such patients necessitates intensive counseling about the risks and proper use of OXYCODONE HCl EXTENDED-RELEASE TABLETS along with intensive monitoring for signs of addiction, abuse, and misuse.

Abuse, or misuse of OXYCODONE HCl EXTENDED-RELEASE TABLETS by crushing, chewing, snorting, or injecting the dissolved product will result in the uncontrolled delivery of oxycodone and can result in overdose and death [see Overdosage (10) ].

Opioid agonists are sought by drug abusers and people with addiction disorders and are subject to criminal diversion. Consider these risks when prescribing or dispensing OXYCODONE HCl EXTENDED-RELEASE TABLETS. Strategies to reduce these risks include prescribing the drug in the smallest appropriate quantity and advising the patient on the proper disposal of unused drug [see Patient Counseling Information (17)]. Contact local state professional licensing board or state controlled substances authority for information on how to prevent and detect abuse or diversion of this product.

5.2 Life-Threatening Respiratory Depression

Serious, life-threatening, or fatal respiratory depression has been reported with the use of modified-release opioids, even when used as recommended. Respiratory depression, if not immediately recognized and treated, may lead to respiratory arrest and death. Management of respiratory depression may include close observation, supportive measures, and use of opioid antagonists, depending on the patient’s clinical status [see Overdosage (10)]. Carbon dioxide (CO2) retention from opioid-induced respiratory depression can exacerbate the sedating effects of opioids.

While serious, life-threatening, or fatal respiratory depression can occur at any time during the use of OXYCODONE HCl EXTENDED-RELEASE TABLETS, the risk is greatest during the initiation of therapy or following a dose increase. Closely monitor patients for respiratory depression when initiating therapy with OXYCODONE HCl EXTENDED-RELEASE TABLETS and following dose increases.

To reduce the risk of respiratory depression, proper dosing and titration of OXYCODONE HCl EXTENDED-RELEASE TABLETS are essential [see Dosage and Administration (2)]. Overestimating the OXYCODONE HCl EXTENDED-RELEASE TABLETS dose when converting patients from another opioid product can result in a fatal overdose with the first dose.

Accidental ingestion of even one dose of OXYCODONE HCl EXTENDED-RELEASE TABLETS, especially by children, can result in respiratory depression and death due to an overdose of oxycodone.

5.3 Neonatal Opioid Withdrawal Syndrome

Prolonged use of OXYCODONE HCl EXTENDED-RELEASE TABLETS during pregnancy can result in withdrawal signs in the neonate. Neonatal opioid withdrawal syndrome, unlike opioid withdrawal syndrome in adults, may be life-threatening if not recognized and treated, and requires management according to protocols developed by neonatology experts. If opioid use is required for a prolonged period in a pregnant woman, advise the patient of the risk of neonatal opioid withdrawal syndrome and ensure that appropriate treatment will be available.

Neonatal opioid withdrawal syndrome presents as irritability, hyperactivity and abnormal sleep pattern, high pitched cry, tremor, vomiting, diarrhea and failure to gain weight. The onset, duration, and severity of neonatal opioid withdrawal syndrome vary based on the specific opioid used, duration of use, timing and amount of last maternal use, and rate of elimination of the drug by the newborn.

5.4 Interactions with Central Nervous System Depressants

Hypotension and profound sedation, coma, or respiratory depression may result if OXYCODONE HCl EXTENDED-RELEASE TABLETS are used concomitantly with other central nervous system (CNS) depressants (e.g., sedatives, anxiolytics, hypnotics, neuroleptics, other opioids).

When considering the use of OXYCODONE HCl EXTENDED-RELEASE TABLETS in a patient taking a CNS depressant, assess the duration of use of the CNS depressant and the patient’s response, including the degree of tolerance that has developed to CNS depression. Additionally, evaluate the patient’s use of alcohol or illicit drugs that can cause CNS depression. If the decision to begin OXYCODONE HCl EXTENDED-RELEASE TABLETS therapy is made, start with 1/3 to 1/2 the usual dose of OXYCODONE HCl EXTENDED-RELEASE TABLETS, monitor patients for signs of sedation and respiratory depression and consider using a lower dose of the concomitant CNS depressant [see Drug Interactions (7.1) and Dosage and Administration (2.6)].

5.5 Use in Elderly, Cachectic, and Debilitated Patients

Life-threatening respiratory depression is more likely to occur in elderly, cachectic, or debilitated patients as they may have altered pharmacokinetics or altered clearance compared to younger, healthier patients. Monitor such patients closely, particularly when initiating and titrating OXYCODONE HCl EXTENDED-RELEASE TABLETS and when OXYCODONE HCl EXTENDED-RELEASE TABLETS are given concomitantly with other drugs that depress respiration [see Warnings and Precautions (5.2)].

5.6 Use in Patients with Chronic Pulmonary Disease

Monitor patients with significant chronic obstructive pulmonary disease or cor pulmonale, and patients having a substantially decreased respiratory reserve, hypoxia, hypercapnia, or pre-existing respiratory depression for respiratory depression, particularly when initiating therapy and titrating with OXYCODONE HCl EXTENDED-RELEASE TABLETS, as in these patients, even usual therapeutic doses of OXYCODONE HCl EXTENDED-RELEASE TABLETS may decrease respiratory drive to the point of apnea [see Warnings and Precautions (5.2)]. Consider the use of alternative non-opioid analgesics in these patients if possible.

5.7 Hypotensive Effects

OXYCODONE HCl EXTENDED-RELEASE TABLETS may cause severe hypotension, including orthostatic hypotension and syncope in ambulatory patients. There is an increased risk in patients whose ability to maintain blood pressure has already been compromised by a reduced blood volume or concurrent administration of certain CNS depressant drugs (e.g., phenothiazines or general anesthetics) [see Drug Interactions (7.1)]. Monitor these patients for signs of hypotension after initiating or titrating the dose of OXYCODONE HCl EXTENDED-RELEASE TABLETS. In patients with circulatory shock, OXYCODONE HCl EXTENDED-RELEASE TABLETS may cause vasodilation that can further reduce cardiac output and blood pressure. Avoid the use of OXYCODONE HCl EXTENDED-RELEASE TABLETS in patients with circulatory shock.

5.8 Use in Patients with Head Injury or Increased Intracranial Pressure

Monitor patients taking OXYCODONE HCl EXTENDED-RELEASE TABLETS who may be susceptible to the intracranial effects of CO2 retention (e.g., those with evidence of increased intracranial pressure or brain tumors) for signs of sedation and respiratory depression, particularly when initiating therapy with OXYCODONE HCl EXTENDED-RELEASE TABLETS. OXYCODONE HCl EXTENDED-RELEASE TABLETS may reduce respiratory drive, and the resultant CO2 retention can further increase intracranial pressure. Opioids may also obscure the clinical course in a patient with a head injury.

Avoid the use of OXYCODONE HCl EXTENDED-RELEASE TABLETS in patients with impaired consciousness or coma.

5.9 Difficulty in Swallowing and Risk for Obstruction in Patients at Risk for a Small Gastrointestinal Lumen

There have been post-marketing reports of difficulty in swallowing OXYCODONE HCl EXTENDED-RELEASE TABLETS. These reports included choking, gagging, regurgitation and tablets stuck in the throat. Instruct patients not to pre-soak, lick or otherwise wet OXYCODONE HCl EXTENDED-RELEASE TABLETS prior to placing in the mouth, and to take one tablet at a time with enough water to ensure complete swallowing immediately after placing in the mouth.

There have been rare post-marketing reports of cases of intestinal obstruction, and exacerbation of diverticulitis, some of which have required medical intervention to remove the tablet. Patients with underlying GI disorders such as esophageal cancer or colon cancer with a small gastrointestinal lumen are at greater risk of developing these complications. Consider use of an alternative analgesic in patients who have difficulty swallowing and patients at risk for underlying GI disorders resulting in a small gastrointestinal lumen.

5.10 Use in Patients with Gastrointestinal Conditions

OXYCODONE HCl EXTENDED-RELEASE TABLETS are contraindicated in patients with GI obstruction, including paralytic ileus. The oxycodone in OXYCODONE HCl EXTENDED-RELEASE TABLETS may cause spasm of the sphincter of Oddi. Monitor patients with biliary tract disease, including acute pancreatitis, for worsening symptoms. Opioids may cause increases in the serum amylase.

5.11 Use in Patients with Convulsive or Seizure Disorders

The oxycodone in OXYCODONE HCl EXTENDED-RELEASE TABLETS may aggravate convulsions in patients with convulsive disorders, and may induce or aggravate seizures in some clinical settings. Monitor patients with a history of seizure disorders for worsened seizure control during OXYCODONE HCl EXTENDED-RELEASE TABLETS therapy.

5.12 Avoidance of Withdrawal

Avoid the use of mixed agonist/antagonist (i.e., pentazocine, nalbuphine, and butorphanol) or partial agonist (buprenorphine) analgesics in patients who have received or are receiving a course of therapy with a full opioid agonist analgesic, including OXYCODONE HCl EXTENDED-RELEASE TABLETS. In these patients, mixed agonist/antagonist and partial agonist analgesics may reduce the analgesic effect and/or may precipitate withdrawal symptoms.

When discontinuing OXYCODONE HCl EXTENDED-RELEASE TABLETS, gradually taper the dose [see Dosage and Administration (2.9)]. Do not abruptly discontinue OXYCODONE HCl EXTENDED-RELEASE TABLETS.

5.13 Driving and Operating Machinery

OXYCODONE HCl EXTENDED-RELEASE TABLETS may impair the mental or physical abilities needed to perform potentially hazardous activities such as driving a car or operating machinery. Warn patients not to drive or operate dangerous machinery unless they are tolerant to the effects of OXYCODONE HCl EXTENDED-RELEASE TABLETS and know how they will react to the medication.

5.14 Cytochrome P450 3A4 Inhibitors and Inducers

Since the CYP3A4 isoenzyme plays a major role in the metabolism of OXYCODONE HCl EXTENDED-RELEASE TABLETS, drugs that alter CYP3A4 activity may cause changes in clearance of oxycodone which could lead to changes in oxycodone plasma concentrations.

Inhibition of CYP3A4 activity by its inhibitors, such as macrolide antibiotics (e.g., erythromycin), azole-antifungal agents (e.g., ketoconazole), and protease inhibitors (e.g., ritonavir), may increase plasma concentrations of oxycodone and prolong opioid effects.

CYP450 inducers, such as rifampin, carbamazepine, and phenytoin, may induce the metabolism of oxycodone and, therefore, may cause increased clearance of the drug which could lead to a decrease in oxycodone plasma concentrations, lack of efficacy or, possibly, development of an abstinence syndrome in a patient who had developed physical dependence to oxycodone.

If co-administration is necessary, caution is advised when initiating OXYCODONE HCl EXTENDED-RELEASE TABLETS treatment in patients currently taking, or discontinuing, CYP3A4 inhibitors or inducers. Evaluate these patients at frequent intervals and consider dose adjustments until stable drug effects are achieved [see Drug Interactions(7.2) and Clinical Pharmacology (12.3)].

5.15 Laboratory Monitoring

Not every urine drug test for “opioids” or “opiates” detects oxycodone reliably, especially those designed for in-office use. Further, many laboratories will report urine drug concentrations below a specified “cut-off” value as “negative”. Therefore, if urine testing for oxycodone is considered in the clinical management of an individual patient, ensure that the sensitivity and specificity of the assay is appropriate, and consider the limitations of the testing used when interpreting results.

6 ADVERSE REACTIONS

The following serious adverse reactions are described elsewhere in the labeling:

Addiction, Abuse, and Misuse [see Warnings and Precautions (5.1)]
Life-Threatening Respiratory Depression [see Warnings and Precautions (5.2)]
Neonatal Opioid Withdrawal Syndrome [see Warnings and Precautions (5.3)]
Interactions with Other CNS Depressants [see Warnings and Precautions (5.4)]
Hypotensive Effects [see Warnings and Precautions (5.7)]
Gastrointestinal Effects [see Warnings and Precautions (5.9, 5.10)]
Seizures [see Warnings and Precautions (5.11)]

6.1 Clinical Trial Experience

Adult Clinical Trial Experience

Because clinical trials are conducted under widely varying conditions, adverse reaction rates observed in the clinical trials of a drug cannot be directly compared to rates in the clinical trials of another drug and may not reflect the rates observed in practice. The safety of OXYCODONE HCl EXTENDED-RELEASE TABLETS was evaluated in double-blind clinical trials involving 713 patients with moderate to severe pain of various etiologies. In open-label studies of cancer pain, 187 patients received OXYCODONE HCl EXTENDED-RELEASE TABLETS in total daily doses ranging from 20 mg to 640 mg per day. The average total daily dose was approximately 105 mg per day.

OXYCODONE HCl EXTENDED-RELEASE TABLETS may increase the risk of serious adverse reactions such as those observed with other opioid analgesics, including respiratory depression, apnea, respiratory arrest, circulatory depression, hypotension, or shock [see Overdosage (10)].

The most common adverse reactions (>5%) reported by patients in clinical trials comparing OXYCODONE HCl EXTENDED-RELEASE TABLETS with placebo are shown in Table 2 below:

TABLE 2: Common Adverse Reactions (>5%)
Adverse Reaction Oxycodone HCl Extended-release Tablets
(n=227) Placebo
(n=45)
(%) (%)
Constipation (23) (7)
Nausea (23) (11)
Somnolence (23) (4)
Dizziness (13) (9)
Pruritus (13) (2)
Vomiting (12) (7)
Headache (7) (7)
Dry Mouth (6) (2)
Asthenia (6) -
Sweating (5) (2)

In clinical trials, the following adverse reactions were reported in patients treated with OXYCODONE HCl EXTENDED-RELEASE TABLETS with an incidence between 1% and 5%:

Gastrointestinal disorders: abdominal pain, diarrhea, dyspepsia, gastritis

General disorders and administration site conditions: chills, fever

Metabolism and nutrition disorders: anorexia

Musculoskeletal and connective tissue disorders: twitching

Psychiatric disorders: abnormal dreams, anxiety, confusion, dysphoria, euphoria, insomnia, nervousness, thought abnormalities

Respiratory, thoracic and mediastinal disorders: dyspnea, hiccups

Skin and subcutaneous tissue disorders: rash

Vascular disorders: postural hypotension

The following adverse reactions occurred in less than 1% of patients involved in clinical trials:

Blood and lymphatic system disorders: lymphadenopathy

Ear and labyrinth disorders: tinnitus

Eye disorders: abnormal vision

Gastrointestinal disorders: dysphagia, eructation, flatulence, gastrointestinal disorder, increased appetite, stomatitis

General disorders and administration site conditions: withdrawal syndrome (with and without seizures), edema, peripheral edema, thirst, malaise, chest pain, facial edema

Injury, poisoning and procedural complications: accidental injury

Investigations: ST depression

Metabolism and nutrition disorders: dehydration

Nervous system disorders: syncope, migraine, abnormal gait, amnesia, hyperkinesia, hypoesthesia, hypotonia, paresthesia, speech disorder, stupor, tremor, vertigo, taste perversion

Psychiatric disorders: depression, agitation, depersonalization, emotional lability, hallucination

Renal and urinary disorders: dysuria, hematuria, polyuria, urinary retention

Reproductive system and breast disorders: impotence

Respiratory, thoracic and mediastinal disorders: cough increased, voice alteration

Skin and subcutaneous tissue disorders: dry skin, exfoliative dermatitis

Clinical Trial Experience in Pediatric Patients 11 Years and Older

The safety of OXYCODONE HCl EXTENDED-RELEASE TABLETS has been evaluated in one clinical trial with 140 patients 11 to 16 years of age. The median duration of treatment was approximately three weeks. The most frequently reported adverse events were vomiting, nausea, headache, pyrexia, and constipation.

Table 3 includes a summary of the incidence of treatment emergent adverse events reported in ≥5% of patients.

Table 3: Incidence of Adverse Reactions Reported in ≥ 5.0% Patients 11 to 16 Years
System Organ Class
Preferred Term 11 to 16 Years
(N=140)
n (%)
Any Adverse Event >= 5% 71 (51)
GASTROINTESTINAL DISORDERS 56 (40)
Vomiting 30 (21)
Nausea 21 (15)
Constipation 13 (9)
Diarrhea 8 (6)
GENERAL DISORDERS AND ADMINISTRATION SITE CONDITIONS 32 (23)
Pyrexia 15 (11)
METABOLISM AND NUTRITION DISORDERS 9 (6)
Decreased appetite 7 (5)
NERVOUS SYSTEM DISORDERS 23 (16)
Pruritus 8 (6)

The following adverse reactions occurred in a clinical trial of OXYCODONE HCl EXTENDED-RELEASE TABLETS in patients 11 to 16 years of age with an incidence between ≥1.0% and < 5.0%. Events are listed within each System/Organ Class.

Blood and lymphatic system disorders: febrile neutropenia, neutropenia

Cardiac disorders: tachycardia

Gastrointestinal disorders: abdominal pain, gastroesophageal reflux disease

General disorders and administration site conditions: fatigue, pain, chills, asthenia

Injury, poisoning, and procedural complications: procedural pain, seroma

Investigations: oxygen saturation decreased, alanine aminotransferase increased, hemoglobin decreased, platelet count decreased, neutrophil count decreased, red blood cell count decreased, weight decreased

Metabolic and nutrition disorders: hypochloremia, hyponatraemia

Musculoskeletal and connective tissue disorders: pain in extremity, musculoskeletal pain

Nervous system disorders: somnolence, hypoesthesia, lethargy, paresthesia

Psychiatric disorders: insomnia, anxiety, depression, agitation

Renal and urinary disorders: dysuria, urinary retention

Respiratory, thoracic, and mediastinal disorders: oropharyngeal pain

Skin and subcutaneous tissue disorders: hyperhidrosis, rash

6.2 Postmarketing Experience

The following adverse reactions have been identified during post-approval use of controlled-release oxycodone: abuse, addiction, aggression, amenorrhea, cholestasis, completed suicide, death, dental caries, increased hepatic enzymes, hyperalgesia, hypogonadism, hyponatremia, ileus, intentional overdose, mood altered, muscular hypertonia, overdose, palpitations (in the context of withdrawal), seizures, suicidal attempt, suicidal ideation, syndrome of inappropriate antidiuretic hormone secretion, and urticaria.

Anaphylaxis has been reported with ingredients contained in OXYCODONE HCl EXTENDED-RELEASE TABLETS. Advise patients how to recognize such a reaction and when to seek medical attention.

In addition to the events listed above, the following have also been reported, potentially due to the swelling and hydrogelling property of the tablet: choking, gagging, regurgitation, tablets stuck in the throat and difficulty swallowing the tablet.

7 DRUG INTERACTIONS

7.1 CNS Depressants

The concomitant use of OXYCODONE HCl EXTENDED-RELEASE TABLETS and other CNS depressants including sedatives, hypnotics, tranquilizers, general anesthetics, phenothiazines, other opioids, and alcohol can increase the risk of respiratory depression, profound sedation, coma, or death. Monitor patients receiving CNS depressants and OXYCODONE HCl EXTENDED-RELEASE TABLETS for signs of respiratory depression, sedation, and hypotension.

When combined therapy with any of the above medications is considered, the dose of one or both agents should be reduced [see Dosage and Administration (2.6) andWarnings and Precautions (5.4)].

7.2 Drugs Affecting Cytochrome P450 Isoenzymes

Inhibitors of CYP3A4 and 2D6

Because the CYP3A4 isoenzyme plays a major role in the metabolism of oxycodone, drugs that inhibit CYP3A4 activity may cause decreased clearance of oxycodone which could lead to an increase in oxycodone plasma concentrations and result in increased or prolonged opioid effects. These effects could be more pronounced with concomitant use of CYP2D6 and 3A4 inhibitors. If co-administration with OXYCODONE HCl EXTENDED-RELEASE TABLETS is necessary, monitor patients for respiratory depression and sedation at frequent intervals and consider dose adjustments until stable drug effects are achieved [see Clinical Pharmacology (12.3)].

Inducers of CYP3A4

CYP450 3A4 inducers may induce the metabolism of oxycodone and, therefore, may cause increased clearance of the drug which could lead to a decrease in oxycodone plasma concentrations, lack of efficacy or, possibly, development of an abstinence syndrome in a patient who had developed physical dependence to oxycodone. If co-administration with OXYCODONE HCl EXTENDED-RELEASE TABLETS is necessary, monitor for signs of opioid withdrawal and consider dose adjustments until stable drug effects are achieved.

After stopping the treatment of a CYP3A4 inducer, as the effects of the inducer decline, the oxycodone plasma concentration will increase which could increase or prolong both the therapeutic and adverse effects, and may cause serious respiratory depression [see Clinical Pharmacology (12.3)].

7.3 Mixed Agonist/Antagonist and Partial Agonists Opioid Analgesics

Mixed agonist/antagonist (i.e., pentazocine, nalbuphine, and butorphanol) and partial agonist (buprenorphine) analgesics may reduce the analgesic effect of oxycodone or precipitate withdrawal symptoms. Avoid the use of mixed agonist/antagonist and partial agonist analgesics in patients receiving OXYCODONE HCl EXTENDED-RELEASE TABLETS.

7.4 Muscle Relaxants

Oxycodone may enhance the neuromuscular blocking action of true skeletal muscle relaxants and produce an increased degree of respiratory depression. Monitor patients receiving muscle relaxants and OXYCODONE HCl EXTENDED-RELEASE TABLETS for signs of respiratory depression that may be greater than otherwise expected.

7.5 Diuretics

Opioids can reduce the efficacy of diuretics by inducing the release of antidiuretic hormone. Opioids may also lead to acute retention of urine by causing spasm of the sphincter of the bladder, particularly in men with enlarged prostates.

7.6 Anticholinergics

Anticholinergics or other medications with anticholinergic activity when used concurrently with opioid analgesics may result in increased risk of urinary retention and/or severe constipation, which may lead to paralytic ileus. Monitor patients for signs of urinary retention or reduced gastric motility when OXYCODONE HCl EXTENDED-RELEASE TABLETS are used concurrently with anticholinergic drugs.

8 USE IN SPECIFIC POPULATIONS

8.1 Pregnancy

Clinical Considerations

Fetal/neonatal adverse reactions

Prolonged use of opioid analgesics during pregnancy for medical or nonmedical purposes can result in physical dependence in the neonate and neonatal opioid withdrawal syndrome shortly after birth. Observe newborns for symptoms of neonatal opioid withdrawal syndrome, such as poor feeding, diarrhea, irritability, tremor, rigidity, and seizures, and manage accordingly [see Warnings and Precautions (5.3)].

Teratogenic Effects - Pregnancy Category C

There are no adequate and well-controlled studies in pregnant women. OXYCODONE HCl EXTENDED-RELEASE TABLETS should be used during pregnancy only if the potential benefit justifies the risk to the fetus.

The effect of oxycodone in human reproduction has not been adequately studied. Studies with oral doses of oxycodone hydrochloride in rats up to 8 mg/kg/day and rabbits up to 125 mg/kg/day, equivalent to 0.5 and 15 times an adult human dose of 160 mg/day, respectively on a mg/m2 basis, did not reveal evidence of harm to the fetus due to oxycodone. In a pre- and postnatal toxicity study, female rats received oxycodone during gestation and lactation. There were no long-term developmental or reproductive effects in the pups [see Nonclinical Toxicology (13.1)].

Non-Teratogenic Effects

Oxycodone hydrochloride was administered orally to female rats during gestation and lactation in a pre- and postnatal toxicity study. There were no drug-related effects on reproductive performance in these females or any long-term developmental or reproductive effects in pups born to these rats. Decreased body weight was found during lactation and the early post-weaning phase in pups nursed by mothers given the highest dose used (6 mg/kg/day, equivalent to approximately 0.4-times an adult human dose of 160 mg/day, on a mg/m2 basis). However, body weight of these pups recovered.

8.2 Labor and Delivery

Opioids cross the placenta and may produce respiratory depression in neonates. OXYCODONE HCl EXTENDED-RELEASE TABLETS are not recommended for use in women immediately prior to labor, when use of shorter-acting analgesics or other analgesic techniques are more appropriate. Opioid analgesics can prolong labor through actions which temporarily reduce the strength, duration and frequency of uterine contractions. However this effect is not consistent and may be offset by an increased rate of cervical dilatation, which tends to shorten labor.

8.3 Nursing Mothers

Oxycodone has been detected in breast milk. Instruct patients not to undertake nursing while receiving OXYCODONE HCl EXTENDED-RELEASE TABLETS. Do not initiate OXYCODONE HCl EXTENDED-RELEASE TABLETS therapy while nursing because of the possibility of sedation or respiratory depression in the infant.

Withdrawal signs can occur in breast-fed infants when maternal administration of an opioid analgesic is stopped, or when breast-feeding is stopped.

8.4 Pediatric Use

The safety and efficacy of OXYCODONE HCl EXTENDED-RELEASE TABLETS have been established in pediatric patients ages 11 to 16 years. Use of OXYCODONE HCl EXTENDED-RELEASE TABLETS is supported by evidence from adequate and well-controlled trials with OXYCODONE HCl EXTENDED-RELEASE TABLETS in adults as well as an open-label study in pediatric patients ages 6 to 16 years. However, there were insufficient numbers of patients less than 11 years of age enrolled in this study to establish the safety of the product in this age group.

The safety of OXYCODONE HCl EXTENDED-RELEASE TABLETS in pediatric patients was evaluated in 155 patients previously receiving and tolerating opioids for at least 5 consecutive days with a minimum of 20 mg per day of oxycodone or its equivalent on the two days immediately preceding dosing with OXYCODONE HCl EXTENDED-RELEASE TABLETS. Patients were started on a total daily dose ranging between 20 mg and 100 mg depending on prior opioid dose.

The most frequent adverse events observed in pediatric patients were vomiting, nausea, headache, pyrexia, and constipation [see Dosage and Administration (2.4), Adverse Reactions (6.1), Clinical Pharmacology (12.3) and Clinical Trials (14)].

8.5 Geriatric Use

In controlled pharmacokinetic studies in elderly subjects (greater than 65 years) the clearance of oxycodone was slightly reduced. Compared to young adults, the plasma concentrations of oxycodone were increased approximately 15% [see Clinical Pharmacology (12.3)]. Of the total number of subjects (445) in clinical studies of oxycodone hydrochloride controlled-release tablets, 148 (33.3%) were age 65 and older (including those age 75 and older) while 40 (9.0%) were age 75 and older. In clinical trials with appropriate initiation of therapy and dose titration, no untoward or unexpected adverse reactions were seen in the elderly patients who received oxycodone hydrochloride controlled-release tablets. Thus, the usual doses and dosing intervals may be appropriate for elderly patients. However, reduce the starting dose to 1/3 to 1/2 the usual dosage in debilitated, non-opioid-tolerant patients. Respiratory depression is the chief risk in elderly or debilitated patients, usually the result of large initial doses in patients who are not tolerant to opioids, or when opioids are given in conjunction with other agents that depress respiration. Titrate the dose of OXYCODONE HCl EXTENDED-RELEASE TABLETS cautiously in these patients.

8.6 Hepatic Impairment

A study of OXYCODONE HCl EXTENDED-RELEASE TABLETS in patients with hepatic impairment demonstrated greater plasma concentrations than those seen at equivalent doses in persons with normal hepatic function. Therefore, in the setting of hepatic impairment, start dosing patients at 1/3 to 1/2 the usual starting dose followed by careful dose titration [see Clinical Pharmacology (12.3)].

8.7 Renal Impairment

In patients with renal impairment, as evidenced by decreased creatinine clearance (<60 mL/min), the concentrations of oxycodone in the plasma are approximately 50% higher than in subjects with normal renal function. Follow a conservative approach to dose initiation and adjust according to the clinical situation [see Clinical Pharmacology (12.3)].

8.8 Gender Differences

In pharmacokinetic studies with OXYCODONE HCl EXTENDED-RELEASE TABLETS, opioid-naïve females demonstrate up to 25% higher average plasma concentrations and greater frequency of typical opioid adverse events than males, even after adjustment for body weight. The clinical relevance of a difference of this magnitude is low for a drug intended for chronic usage at individualized dosages, and there was no male/female difference detected for efficacy or adverse events in clinical trials.

9 DRUG ABUSE AND DEPENDENCE

9.1 Controlled Substance

OXYCODONE HCl EXTENDED-RELEASE TABLETS contain oxycodone, a Schedule II controlled substance with a high potential for abuse similar to other opioids includingfentanyl, hydromorphone, methadone, morphine, and oxymorphone. OXYCODONE HCl EXTENDED-RELEASE TABLETS can be abused and are subject to misuse, addiction, and criminal diversion [see Warnings and Precautions (5.1)].

The high drug content in extended-release formulations adds to the risk of adverse outcomes from abuse and misuse.

9.2 Abuse

All patients treated with opioids require careful monitoring for signs of abuse and addiction, since use of opioid analgesic products carries the risk of addiction even under appropriate medical use.

Drug abuse is the intentional non-therapeutic use of an over-the-counter or prescription drug, even once, for its rewarding psychological or physiological effects. Drug abuse includes, but is not limited to, the following examples: the use of a prescription or over-the-counter drug to get “high”, or the use of steroids for performance enhancement and muscle build up.

Drug addiction is a cluster of behavioral, cognitive, and physiological phenomena that develop after repeated substance use and include: a strong desire to take the drug, difficulties in controlling its use, persisting in its use despite harmful consequences, a higher priority given to drug use than to other activities and obligations, increased tolerance, and sometimes a physical withdrawal.

"Drug-seeking" behavior is very common to addicts and drug abusers. Drug-seeking tactics include emergency calls or visits near the end of office hours, refusal to undergo appropriate examination, testing or referral, repeated claims of loss of prescriptions, tampering with prescriptions and reluctance to provide prior medical records or contact information for other treating physician(s). “Doctor shopping” (visiting multiple prescribers) to obtain additional prescriptions is common among drug abusers and people suffering from untreated addiction. Preoccupation with achieving adequate pain relief can be appropriate behavior in a patient with poor pain control.

Abuse and addiction are separate and distinct from physical dependence and tolerance. Physicians should be aware that addiction may not be accompanied by concurrent tolerance and symptoms of physical dependence in all addicts. In addition, abuse of opioids can occur in the absence of true addiction.

OXYCODONE HCl EXTENDED-RELEASE TABLETS, like other opioids, can be diverted for non-medical use into illicit channels of distribution. Careful recordkeeping of prescribing information, including quantity, frequency, and renewal requests as required by state law, is strongly advised.

Proper assessment of the patient, proper prescribing practices, periodic reevaluation of therapy, and proper dispensing and storage are appropriate measures that help to reduce abuse of opioid drugs.

Risks Specific to Abuse of OXYCODONE HCl EXTENDED-RELEASE TABLETS

OXYCODONE HCl EXTENDED-RELEASE TABLETS are for oral use only. Abuse of OXYCODONE HCl EXTENDED-RELEASE TABLETS poses a risk of overdose and death. The risk is increased with concurrent use of OXYCODONE HCl EXTENDED-RELEASE TABLETS with alcohol and other central nervous system depressants. Taking cut, broken, chewed, crushed, or dissolved OXYCODONE HCl EXTENDED-RELEASE TABLETS enhances drug release and increases the risk of overdose and death.

With parenteral abuse, the inactive ingredients in OXYCODONE HCl EXTENDED-RELEASE TABLETS can be expected to result in local tissue necrosis, infection, pulmonary granulomas, and increased risk of endocarditis and valvular heart injury. Parenteral drug abuse is commonly associated with transmission of infectious diseases, such as hepatitis and HIV.

Abuse Deterrence Studies

OXYCODONE HCl EXTENDED-RELEASE TABLETS are formulated with inactive ingredients intended to make the tablet more difficult to manipulate for misuse and abuse. For the purposes of describing the results of studies of the abuse-deterrent characteristics of OXYCODONE HCl EXTENDED-RELEASE TABLETS resulting from a change in formulation, in this section, the original formulation of OXYCODONE HCl EXTENDED-RELEASE TABLETS, which is no longer marketed, will be referred to as “original OxyContin” and the reformulated, currently marketed product will be referred to as “OXYCODONE HCl EXTENDED-RELEASE TABLETS".

In Vitro Testing

In vitro physical and chemical tablet manipulation studies were performed to evaluate the success of different extraction methods in defeating the extended-release formulation. Results support that, relative to original OxyContin, there is an increase in the ability of OXYCODONE HCl EXTENDED-RELEASE TABLETS to resist crushing, breaking, and dissolution using a variety of tools and solvents. The results of these studies also support this finding for OXYCODONE HCl EXTENDED-RELEASE TABLETS relative to an immediate-release oxycodone. When subjected to an aqueous environment, OXYCODONE HCl EXTENDED-RELEASE TABLETS gradually form a viscous hydrogel (i.e., a gelatinous mass) that resists passage through a needle.

Clinical Studies

In a randomized, double-blind, placebo-controlled 5-period crossover pharmacodynamic study, 30 recreational opioid users with a history of intranasal drug abuse received intranasally administered active and placebo drug treatments. The five treatment arms were finely crushed OXYCODONE HCl EXTENDED-RELEASE TABLETS 30 mg tablets, coarsely crushed OXYCODONE HCl EXTENDED-RELEASE TABLETS 30 mg tablets, finely crushed original OxyContin 30 mg tablets, powdered oxycodone HCl 30 mg, and placebo. Data for finely crushed OXYCODONE HCl EXTENDED-RELEASE TABLETS, finely crushed original OxyContin, and powdered oxycodone HCl are described below.

Drug liking was measured on a bipolar drug liking scale of 0 to 100 where 50 represents a neutral response of neither liking nor disliking, 0 represents maximum disliking and 100 represents maximum liking. Response to whether the subject would take the study drug again was also measured on a bipolar scale of 0 to 100 where 50 represents a neutral response, 0 represents the strongest negative response (“definitely would not take drug again”) and 100 represents the strongest positive response (“definitely would take drug again”).

Twenty-seven of the subjects completed the study. Incomplete dosing due to granules falling from the subjects’ nostrils occurred in 34% (n = 10) of subjects with finely crushed OXYCODONE HCl EXTENDED-RELEASE TABLETS, compared with 7% (n = 2) of subjects with finely crushed original OxyContin and no subjects with powdered oxycodone HCl.

The intranasal administration of finely crushed OXYCODONE HCl EXTENDED-RELEASE TABLETS was associated with a numerically lower mean and median drug liking score and a lower mean and median score for take drug again, compared to finely crushed original OxyContin or powdered oxycodone HCl as summarized in Table 4.

Table 4: Summary of Maximum Drug Liking (Emax) Data Following Intranasal Administration

*
Bipolar scale (0 = maximum negative response, 50 = neutral response, 100 = maximum positive response)

VAS Scale
(100 mm)*

OXYCODONE HCl
EXTENDED-RELEASE TABLETS
(finely crushed)

Original OxyContin (finely crushed)

Oxycodone HCl

(powdered)
Drug Liking Mean (SE) 80.4 (3.9) 94.0 (2.7) 89.3 (3.1)
Median (Range) 88 (36-100) 100 (51-100) 100 (50-100)
Take Drug Again Mean (SE) 64.0 (7.1) 89.6 (3.9) 86.6 (4.4)
Median (Range) 78 (0-100) 100 (20-100) 100 (0-100)

Figure 1 demonstrates a comparison of drug liking for finely crushed OXYCODONE HCl EXTENDED-RELEASE TABLETS compared to powdered oxycodone HCl in subjects who received both treatments. The Y-axis represents the percent of subjects attaining a percent reduction in drug liking for OXYCODONE HCl EXTENDED-RELEASE TABLETS vs. oxycodone HCl powder greater than or equal to the value on the X-axis. Approximately 44% (n = 12) had no reduction in liking with OXYCODONE HCl EXTENDED-RELEASE TABLETS relative to oxycodone HCl. Approximately 56% (n = 15) of subjects had some reduction in drug liking with OXYCODONE HCl EXTENDED-RELEASE TABLETS relative to oxycodone HCl. Thirty-three percent (n = 9) of subjects had a reduction of at least 30% in drug liking with OXYCODONE HCl EXTENDED-RELEASE TABLETS compared to oxycodone HCl, and approximately 22% (n = 6) of subjects had a reduction of at least 50% in drug liking with OXYCODONE HCl EXTENDED-RELEASE TABLETS compared to oxycodone HCl.

Figure 1: Percent Reduction Profiles for Emax of Drug Liking VAS for OXYCODONE HCl EXTENDED-RELEASE TABLETS vs. oxycodone HCl, N=27 Following Intranasal Administration

[figure 1]

The results of a similar analysis of drug liking for finely crushed OXYCODONE HCl EXTENDED-RELEASE TABLETS relative to finely crushed original OxyContin were comparable to the results of finely crushed OXYCODONE HCl EXTENDED-RELEASE TABLETS relative to powdered oxycodone HCl. Approximately 43% (n = 12) of subjects had no reduction in liking with OXYCODONE HCl EXTENDED-RELEASE TABLETS relative to original OxyContin. Approximately 57% (n = 16) of subjects had some reduction in drug liking, 36% (n = 10) of subjects had a reduction of at least 30% in drug liking, and approximately 29% (n = 8) of subjects had a reduction of at least 50% in drug liking with OXYCODONE HCl EXTENDED-RELEASE TABLETS compared to original OxyContin.

Summary

The in vitro data demonstrate that OXYCODONE HCl EXTENDED-RELEASE TABLETS have physicochemical properties expected to make abuse via injection difficult. The data from the clinical study, along with support from the invitro data, also indicate that OXYCODONE HCl EXTENDED-RELEASE TABLETS have physicochemical properties that are expected to reduce abuse via the intranasal route. However, abuse of OXYCODONE HCl EXTENDED-RELEASE TABLETS by these routes, as well as by the oral route, is still possible.

Additional data, including epidemiological data, when available, may provide further information on the impact of the current formulation of OXYCODONE HCl EXTENDED-RELEASE TABLETS on the abuse liability of the drug. Accordingly, this section may be updated in the future as appropriate.

OXYCODONE HCl EXTENDED-RELEASE TABLETS contain oxycodone, an opioid agonist and Schedule II controlled substance with an abuse liability similar to other opioid agonists, legal or illicit, including fentanyl, hydromorphone, methadone, morphine, and oxymorphone. OXYCODONE HCl EXTENDED-RELEASE TABLETS can be abused and are subject to misuse, addiction, and criminal diversion [see Warnings and Precautions (5.1) and Drug Abuse and Dependence (9.1)].

9.3 Dependence

Both tolerance and physical dependence can develop during chronic opioid therapy. Tolerance is the need for increasing doses of opioids to maintain a defined effect such as analgesia (in the absence of disease progression or other external factors). Tolerance may occur to both the desired and undesired effects of drugs, and may develop at different rates for different effects.

Physical dependence results in withdrawal symptoms after abrupt discontinuation or a significant dose reduction of a drug. Withdrawal also may be precipitated through the administration of drugs with opioid antagonist activity, e.g., naloxone, nalmefene, mixed agonist/antagonist analgesics (pentazocine, butorphanol, nalbuphine), or partial agonists (buprenorphine). Physical dependence may not occur to a clinically significant degree until after several days to weeks of continued opioid usage.

OXYCODONE HCl EXTENDED-RELEASE TABLETS should not be abruptly discontinued [see Dosage and Administration (2.9)]. If OXYCODONE HCl EXTENDED-RELEASE TABLETS are abruptly discontinued in a physically-dependent patient, an abstinence syndrome may occur. Some or all of the following can characterize this syndrome: restlessness, lacrimation, rhinorrhea, yawning, perspiration, chills, myalgia, and mydriasis. Other signs and symptoms also may develop, including: irritability, anxiety, backache, joint pain, weakness, abdominal cramps, insomnia, nausea, anorexia, vomiting, diarrhea, or increased blood pressure, respiratory rate, or heart rate.

Infants born to mothers physically dependent on opioids will also be physically dependent and may exhibit respiratory difficulties and withdrawal signs [see Use in Specific Populations (8.1)].

10 OVERDOSAGE

Clinical Presentation

Acute overdosage with OXYCODONE HCl EXTENDED-RELEASE TABLETS can be manifested by respiratory depression, somnolence progressing to stupor or coma, skeletal muscle flaccidity, cold and clammy skin, constricted pupils, and in some cases, pulmonary edema, bradycardia, hypotension, partial or complete airway obstruction, atypical snoring and death. Marked mydriasis rather than miosis may be seen due to severe hypoxia in overdose situations.

Treatment of Overdose

In case of overdose, priorities are the reestablishment of a patent and protected airway and institution of assisted or controlled ventilation if needed. Employ other supportive measures (including oxygen, vasopressors) in the management of circulatory shock and pulmonary edema as indicated. Cardiac arrest or arrhythmias will require advanced life support techniques.

The opioid antagonists, naloxone or nalmefene, are specific antidotes to respiratory depression resulting from opioid overdose. Opioid antagonists should not be administered in the absence of clinically significant respiratory or circulatory depression secondary to oxycodone overdose. Such agents should be administered cautiously to persons who are known or suspected to be physically dependent on OXYCODONE HCl EXTENDED-RELEASE TABLETS. In such cases, an abrupt or complete reversal of opioid effects may precipitate an acute withdrawal syndrome.

Because the duration of reversal would be expected to be less than the duration of action of oxycodone in OXYCODONE HCl EXTENDED-RELEASE TABLETS, carefully monitor the patient until spontaneous respiration is reliably reestablished. OXYCODONE HCl EXTENDED-RELEASE TABLETS will continue to release oxycodone and add to the oxycodone load for 24 to 48 hours or longer following ingestion necessitating prolonged monitoring. If the response to opioid antagonists is suboptimal or not sustained, additional antagonist should be administered as directed in the product’s prescribing information.

In an individual physically dependent on opioids, administration of the usual dose of the antagonist will precipitate an acute withdrawal syndrome. The severity of the withdrawal symptoms experienced will depend on the degree of physical dependence and the dose of the antagonist administered. If a decision is made to treat serious respiratory depression in the physically dependent patient, administration of the antagonist should be begun with care and by titration with smaller than usual doses of the antagonist.

11 DESCRIPTION

OXYCODONE HCl EXTENDED-RELEASE TABLETS are an opioid analgesic supplied in 10 mg, 15 mg, 20 mg, 30 mg, 40 mg, 60 mg, and 80 mg tablets for oral administration. The tablet strengths describe the amount of oxycodone per tablet as the hydrochloride salt. The structural formula for oxycodone hydrochloride is as follows:

[chemical structure]

C18H21NO4 ∙ HCl MW 351.83

The chemical name is 4, 5a-epoxy-14-hydroxy-3-methoxy-17-methylmorphinan-6-one hydrochloride.

Oxycodone is a white, odorless crystalline powder derived from the opium alkaloid, thebaine. Oxycodone hydrochloride dissolves in water (1 g in 6 to 7 mL). It is slightly soluble in alcohol (octanol water partition coefficient 0.7).

The 10 mg, 15 mg, 20 mg, 30 mg, 40 mg, 60 mg and 80 mg tablets contain the following inactive ingredients: butylated hydroxytoluene (BHT), hypromellose, polyethylene glycol 400, polyethylene oxide, magnesium stearate, titanium dioxide.

The 10 mg tablets also contain hydroxypropyl cellulose.

The 15 mg tablets also contain black iron oxide, yellow iron oxide, and red iron oxide.

The 20 mg tablets also contain polysorbate 80 and red iron oxide.

The 30 mg tablets also contain polysorbate 80, red iron oxide, yellow iron oxide, and black iron oxide.

The 40 mg tablets also contain polysorbate 80 and yellow iron oxide.

The 60 mg tablets also contain polysorbate 80, red iron oxide and black iron oxide.

The 80 mg tablets also contain hydroxypropyl cellulose, yellow iron oxide and FD&C Blue #2/Indigo Carmine Aluminum Lake.

12 CLINICAL PHARMACOLOGY

Oxycodone hydrochloride is a full opioid agonist and is relatively selective for the mu receptor, although it can bind to other opioid receptors at higher doses. The principal therapeutic action of oxycodone is analgesia. Like all full opioid agonists, there is no ceiling effect to analgesia for oxycodone. Clinically, dosage is titrated to provide adequate analgesia and may be limited by adverse reactions, including respiratory and CNS depression.

12.1 Mechanism of Action

Central Nervous System

The precise mechanism of the analgesic action is unknown. However, specific CNS opioid receptors for endogenous compounds with opioid-like activity have been identified throughout the brain and spinal cord and are thought to play a role in the analgesic effects of this drug.

12.2 Pharmacodynamics

A single-dose, double-blind, placebo- and dose-controlled study was conducted using OXYCODONE HCl EXTENDED-RELEASE TABLETS (10, 20, and 30 mg) in an analgesic pain model involving 182 patients with moderate to severe pain. OXYCODONE HCl EXTENDED-RELEASE TABLETS doses of 20 mg and 30 mg produced statistically significant pain reduction compared to placebo.

Effects on the Central Nervous System

Oxycodone produces respiratory depression by direct action on brain stem respiratory centers. The respiratory depression involves both a reduction in the responsiveness of the brain stem respiratory centers to increases in CO2 tension and to electrical stimulation.

Oxycodone depresses the cough reflex by direct effect on the cough center in the medulla. Antitussive effects may occur with doses lower than those usually required for analgesia.

Oxycodone causes miosis, even in total darkness. Pinpoint pupils are a sign of opioid overdose but are not pathognomonic (e.g., pontine lesions of hemorrhagic or ischemic origin may produce similar findings). Marked mydriasis rather than miosis may be seen with hypoxia in the setting of oxycodone overdose [seeOverdosage (10)].

Effects on the Gastrointestinal Tract and Other Smooth Muscle

Oxycodone causes a reduction in motility associated with an increase in smooth muscle tone in the antrum of the stomach and duodenum. Digestion of food in the small intestine is delayed and propulsive contractions are decreased. Propulsive peristaltic waves in the colon are decreased, while tone may be increased to the point of spasm resulting in constipation. Other opioid-induced effects may include a reduction in gastric, biliary and pancreatic secretions, spasm of sphincter of Oddi, and transient elevations in serum amylase.

Effects on the Cardiovascular System

Oxycodone may produce release of histamine with or without associated peripheral vasodilation. Manifestations of histamine release and/or peripheral vasodilation may include pruritus, flushing, red eyes, sweating, and/or orthostatic hypotension.

Effects on the Endocrine System

Opioids inhibit the secretion of ACTH, cortisol, testosterone, and luteinizing hormone (LH) in humans. They also stimulate prolactin, growth hormone (GH) secretion, and pancreatic secretion of insulin and glucagon.

Effects on the Immune System

Opioids have been shown to have a variety of effects on components of the immune system in in vitro and animal models. The clinical significance of these findings is unknown. Overall, the effects of opioids appear to be modestly immunosuppressive.

Concentration –Efficacy Relationships

Studies in normal volunteers and patients reveal predictable relationships between oxycodone dosage and plasma oxycodone concentrations, as well as between concentration and certain expected opioid effects, such as pupillary constriction, sedation, overall subjective “drug effect”, analgesia and feelings of relaxation.

The minimum effective analgesic concentration will vary widely among patients, especially among patients who have been previously treated with potent agonist opioids. As a result, patients must be treated with individualized titration of dosage to the desired effect. The minimum effective analgesic concentration of oxycodone for any individual patient may increase over time due to an increase in pain, the development of a new pain syndrome and/or the development of analgesic tolerance.

Concentration –Adverse Reaction Relationships

There is a relationship between increasing oxycodone plasma concentration and increasing frequency of dose-related opioid adverse reactions such as nausea, vomiting, CNS effects, and respiratory depression. In opioid-tolerant patients, the situation may be altered by the development of tolerance to opioid-related side effects.

The dose of OXYCODONE HCl EXTENDED-RELEASE TABLETS must be individualized because the effective analgesic dose for some patients will be too high to be tolerated by other patients [see Dosage and Administration (2.1)].

12.3 Pharmacokinetics

The activity of OXYCODONE HCl EXTENDED-RELEASE TABLETS is primarily due to the parent drug oxycodone. OXYCODONE HCl EXTENDED-RELEASE TABLETS are designed to provide delivery of oxycodone over 12 hours.

Cutting, breaking, chewing, crushing or dissolving OXYCODONE HCl EXTENDED-RELEASE TABLETS impairs the controlled-release delivery mechanism and results in the rapid release and absorption of a potentially fatal dose of oxycodone.

Oxycodone release from OXYCODONE HCl EXTENDED-RELEASE TABLETS is pH independent. The oral bioavailability of oxycodone is 60% to 87%. The relative oral bioavailability of oxycodone from OXYCODONE HCl EXTENDED-RELEASE TABLETS to that from immediate-release oral dosage forms is 100%. Upon repeated dosing with OXYCODONE HCl EXTENDED-RELEASE TABLETS in healthy subjects in pharmacokinetic studies, steady-state levels were achieved within 24-36 hours. Oxycodone is extensively metabolized and eliminated primarily in the urine as both conjugated and unconjugated metabolites. The apparent elimination half-life (t½) of oxycodone following the administration of OXYCODONE HCl EXTENDED-RELEASE TABLETS was 4.5 hours compared to 3.2 hours for immediate-release oxycodone.

Absorption

About 60% to 87% of an oral dose of oxycodone reaches the central compartment in comparison to a parenteral dose. This high oral bioavailability is due to low pre-systemic and/or first-pass metabolism.

Plasma Oxycodone Concentration over Time

Dose proportionality has been established for OXYCODONE HCl EXTENDED-RELEASE TABLETS 10 mg, 15 mg, 20 mg, 30 mg, 40 mg, 60 mg, and 80 mg tablet strengths for both peak plasma concentrations (Cmax) and extent of absorption (AUC) (see Table 5). Given the short elimination t½ of oxycodone, steady-state plasma concentrations of oxycodone are achieved within 24-36 hours of initiation of dosing with OXYCODONE HCl EXTENDED-RELEASE TABLETS. In a study comparing 10 mg of OXYCODONE HCl EXTENDED-RELEASE TABLETS every 12 hours to 5 mg of immediate-release oxycodone every 6 hours, the two treatments were found to be equivalent for AUC and Cmax, and similar for Cmin (trough) concentrations.

TABLE 5 Mean [% coefficient of variation]
Regimen Dosage
Form AUC
(ng∙hr/mL)* Cmax
(ng/mL) Tmax
(hr)

*
for single-dose AUC = AUC 0-inf
†
data obtained while subjects received naltrexone, which can enhance absorption

Single Dose† 10 mg 136 [27] 11.5 [27] 5.11 [21]
15 mg 196 [28] 16.8 [29] 4.59 [19]
20 mg 248 [25] 22.7 [25] 4.63 [22]
30 mg 377 [24] 34.6 [21] 4.61 [19]
40 mg 497 [27] 47.4 [30] 4.40 [22]
60 mg 705 [22] 64.6 [24] 4.15 [26]
80 mg 908 [21] 87.1 [29] 4.27 [26]

Food Effects

Food has no significant effect on the extent of absorption of oxycodone from OXYCODONE HCl EXTENDED-RELEASE TABLETS.

Distribution

Following intravenous administration, the steady-state volume of distribution (Vss) for oxycodone was 2.6 L/kg. Oxycodone binding to plasma protein at 37°C and a pH of 7.4 was about 45%. Once absorbed, oxycodone is distributed to skeletal muscle, liver, intestinal tract, lungs, spleen, and brain. Oxycodone has been found in breast milk [see Use in Specific Populations (8.3)].

Metabolism

Oxycodone is extensively metabolized by multiple metabolic pathways to produce noroxycodone, oxymorphone and noroxymorphone, which are subsequently glucuronidated. Noroxycodone and noroxymorphone are the major circulating metabolites. CYP3A mediated N-demethylation to noroxycodone is the primary metabolic pathway of oxycodone with a lower contribution from CYP2D6 mediated O-demethylation to oxymorphone. Therefore, the formation of these and related metabolites can, in theory, be affected by other drugs [see Drug Interactions (7.3)].

Noroxycodone exhibits very weak anti-nociceptive potency compared to oxycodone, however, it undergoes further oxidation to produce noroxymorphone, which is active at opioid receptors. Although noroxymorphone is an active metabolite and present at relatively high concentrations in circulation, it does not appear to cross the blood-brain barrier to a significant extent. Oxymorphone is present in the plasma only at low concentrations and undergoes further metabolism to form its glucuronide and noroxymorphone. Oxymorphone has been shown to be active and possessing analgesic activity but its contribution to analgesia following oxycodone administration is thought to be clinically insignificant. Other metabolites (α- and ß-oxycodol, noroxycodol and oxymorphol) may be present at very low concentrations and demonstrate limited penetration into the brain as compared to oxycodone. The enzymes responsible for keto-reduction and glucuronidation pathways in oxycodone metabolism have not been established.

Excretion

Oxycodone and its metabolites are excreted primarily via the kidney. The amounts measured in the urine have been reported as follows: free and conjugated oxycodone 8.9%, free noroxycodone 23%, free oxymorphone less than 1%, conjugated oxymorphone 10%, free and conjugated noroxymorphone 14%, reduced free and conjugated metabolites up to 18%. The total plasma clearance was approximately 1.4 L/min in adults.

Special Populations

Geriatric Use

The plasma concentrations of oxycodone are only nominally affected by age, being 15% greater in elderly as compared to young subjects (age 21-45).

Gender

Across individual pharmacokinetic studies, average plasma oxycodone concentrations for female subjects were up to 25% higher than for male subjects on a body weight-adjusted basis. The reason for this difference is unknown [see Use in Specific Populations (8.8)].

Renal Impairment

Data from a pharmacokinetic study involving 13 patients with mild to severe renal dysfunction (creatinine clearance <60 mL/min) showed peak plasma oxycodone and noroxycodone concentrations 50% and 20% higher, respectively, and AUC values for oxycodone, noroxycodone, and oxymorphone 60%, 50%, and 40% higher than normal subjects, respectively. This was accompanied by an increase in sedation but not by differences in respiratory rate, pupillary constriction, or several other measures of drug effect. There was an increase in mean elimination t½ for oxycodone of 1 hour.

Hepatic Impairment

Data from a study involving 24 patients with mild to moderate hepatic dysfunction show peak plasma oxycodone and noroxycodone concentrations 50% and 20% higher, respectively, than healthy subjects. AUC values are 95% and 65% higher, respectively. Oxymorphone peak plasma concentrations and AUC values are lower by 30% and 40%. These differences are accompanied by increases in some, but not other, drug effects. The mean elimination t½ for oxycodone increased by 2.3 hours.

Pediatric Use

In the pediatric age group of 11 years of age and older, systemic exposure of oxycodone is expected to be similar to adults at any given dose of OXYCODONE HCl EXTENDED-RELEASE TABLETS.

Drug-Drug Interactions

CYP3A4 Inhibitors

CYP3A4 is the major isoenzyme involved in noroxycodone formation. Co-administration of OXYCODONE HCl EXTENDED-RELEASE TABLETS (10 mg single dose) and the CYP3A4 inhibitor ketoconazole (200 mg BID) increased oxycodone AUC and Cmax by 170% and 100%, respectively [see Drug Interactions (7.2)].

CYP3A4 Inducers

A published study showed that the co-administration of rifampin, a drug metabolizing enzyme inducer, decreased oxycodone AUC and Cmax values by 86% and 63%, respectively [see Drug Interactions (7.2)].

CYP2D6 Inhibitors

Oxycodone is metabolized in part to oxymorphone via CYP2D6. While this pathway may be blocked by a variety of drugs such as certain cardiovascular drugs (e.g., quinidine) and antidepressants (e.g., fluoxetine), such blockade has not been shown to be of clinical significance with OXYCODONE HCl EXTENDED-RELEASE TABLETS [see Drug Interactions (7.2)].

13 NONCLINICAL TOXICOLOGY

13.1 Carcinogenesis, Mutagenesis, Impairment of Fertility

Carcinogenesis

No animal studies to evaluate the carcinogenic potential of oxycodone have been conducted.

Mutagenesis

Oxycodone was genotoxic in the mouse lymphoma assay at concentrations of 50 mcg/mL or greater with metabolic activation and at 400 mcg/mL or greater without metabolic activation. Clastogenicity was observed with oxycodone in the presence of metabolic activation in one chromosomal aberration assay in human lymphocytes at concentrations greater than or equal to 1250 mcg/mL at 24 but not 48 hours of exposure. In a second chromosomal aberration assay with human lymphocytes, no structural clastogenicity was observed either with or without metabolic activation; however, in the absence of metabolic activation, oxycodone increased numerical chromosomal aberrations (polyploidy). Oxycodone was not genotoxic in the following assays: Ames S. typhimurium and E. coli test with and without metabolic activation at concentrations up to 5000 µg/plate, chromosomal aberration test in human lymphocytes (in the absence of metabolic activation) at concentrations up to 1500 µg/mL, and with activation after 48 hours of exposure at concentrations up to 5000 µg/mL, and in the in vivo bone marrow micronucleus assay in mice (at plasma levels up to 48 µg/mL).

Impairment of Fertility

In a study of reproductive performance, rats were administered a once daily gavage dose of the vehicle or oxycodone hydrochloride (0.5, 2, and 8 mg/kg/day). Male rats were dosed for 28 days before cohabitation with females, during the cohabitation and until necropsy (2-3 weeks post-cohabitation). Females were dosed for 14 days before cohabitation with males, during cohabitation and up to gestation day 6. Oxycodone hydrochloride did not affect reproductive function in male or female rats at any dose tested (≤ 8 mg/kg/day).

14 CLINICAL STUDIES

Adult clinical study

A double-blind, placebo-controlled, fixed-dose, parallel group, two-week study was conducted in 133 patients with persistent, moderate to severe pain, who were judged as having inadequate pain control with their current therapy. In this study, OXYCODONE HCl EXTENDED-RELEASE TABLETS 20 mg, but not 10 mg, were statistically significant in pain reduction compared with placebo.

Pediatric clinical study

OXYCODONE HCl EXTENDED-RELEASE TABLETS has been evaluated in an open-label clinical trial of 155 opioid-tolerant pediatric patients with moderate to severe chronic pain. The mean duration of therapy was 20.7 days (range 1 to 43 days). The starting total daily doses ranged from 20 mg to 100 mg based on the patient’s prior opioid dose. The mean daily dose was 33.30 mg (range 20 to 140 mg/day). In an extension study, 23 of the 155 patients were treated beyond four weeks, including 13 for 28 weeks. Too few patients less than 11 years were enrolled in the clinical trial to provide meaningful safety data in this age group.

16 HOW SUPPLIED/STORAGE AND HANDLING

OXYCODONE HCl EXTENDED-RELEASE TABLETS (oxycodone hydrochloride) extended-release tablets 10 mg are film-coated, round, white-colored, bi-convex tablets debossed with OP on one side and 10 on the other and are supplied as child-resistant closure, opaque plastic bottles of 100 (NDC 0115-1556-01)

OXYCODONE HCl EXTENDED-RELEASE TABLETS (oxycodone hydrochloride) extended-release tablets 15 mg are film-coated, round, gray-colored, bi-convex tablets debossed with OP on one side and 15 on the other and are supplied as child-resistant closure, opaque plastic bottles of 100 (NDC 0115-1557-01)

OXYCODONE HCl EXTENDED-RELEASE TABLETS (oxycodone hydrochloride) extended-release tablets 20 mg are film-coated, round, pink-colored, bi-convex tablets debossed with OP on one side and 20 on the other and are supplied as child-resistant closure, opaque plastic bottles of 100 (NDC 0115-1558-01)

OXYCODONE HCl EXTENDED-RELEASE TABLETS (oxycodone hydrochloride) extended-release tablets 30 mg are film-coated, round, brown-colored, bi-convex tablets debossed with OP on one side and 30 on the other and are supplied as child-resistant closure, opaque plastic bottles of 100 (NDC 0115-1559-01)

OXYCODONE HCl EXTENDED-RELEASE TABLETS (oxycodone hydrochloride) extended-release tablets 40 mg are film-coated, round, yellow-colored, bi-convex tablets debossed with OP on one side and 40 on the other and are supplied as child-resistant closure, opaque plastic bottles of 100 (NDC 0115-1560-01)

OXYCODONE HCl EXTENDED-RELEASE TABLETS (oxycodone hydrochloride) extended-release tablets 60 mg are film-coated, round, red-colored, bi-convex tablets debossed with OP on one side and 60 on the other and are supplied as child-resistant closure, opaque plastic bottles of 100 (NDC 0115-1561-01)

OXYCODONE HCl EXTENDED-RELEASE TABLETS (oxycodone hydrochloride) extended-release tablets 80 mg are film-coated, round, green-colored, bi-convex tablets debossed with OP on one side and 80 on the other and are supplied as child-resistant closure, opaque plastic bottles of 100 (NDC 0115-1562-01)

Store at 25°C (77°F); excursions permitted between 15°-30°C (59°-86°F).

Dispense in tight, light-resistant container.

CAUTION

DEA FORM REQUIRED

17 PATIENT COUNSELING INFORMATION

Advise the patient to read the FDA-approved patient labeling (Medication Guide).

Addiction, Abuseand Misuse

Inform patients that the use of OXYCODONE HCl EXTENDED-RELEASE TABLETS, even when taken as recommended, can result in addiction, abuse, and misuse, which can lead to overdose and death [see Warnings and Precautions (5.1)]. Instruct patients not to share OXYCODONE HCl EXTENDED-RELEASE TABLETS with others and to take steps to protect OXYCODONE HCl EXTENDED-RELEASE TABLETS from theft or misuse.

Life-Threatening Respiratory Depression

Inform patients of the risk of life-threatening respiratory depression including information that the risk is greatest when starting OXYCODONE HCl EXTENDED-RELEASE TABLETS or when the dose is increased and that it can occur even at recommended doses [see Warnings and Precautions (5.2)]. Advise patients how to recognize respiratory depression and to seek medical attention if breathing difficulties develop.

To guard against excessive exposure to OXYCODONE HCl EXTENDED-RELEASE TABLETS by young children, advise caregivers to strictly adhere to recommended OXYCODONE HCl EXTENDED-RELEASE TABLETS dosing.

Accidental Ingestion

Inform patients that accidental ingestion, especially in children, may result in respiratory depression or death [see Warnings and Precautions (5.2)]. Instruct patients to take steps to store OXYCODONE HCl EXTENDED-RELEASE TABLETS securely and to dispose of unused OXYCODONE HCl EXTENDED-RELEASE TABLETS by flushing the tablets down the toilet.

Neonatal Opioid Withdrawal Syndrome

Inform female patients of reproductive potential that prolonged use of OXYCODONE HCl EXTENDED-RELEASE TABLETS during pregnancy can result in neonatal opioid withdrawal syndrome, which may be life-threatening if not recognized and treated [see Warnings and Precautions (5.3)].

Interactions with Alcohol and other CNS Depressants

Inform patients that potentially serious additive effects may occur if OXYCODONE HCl EXTENDED-RELEASE TABLETS are used with other CNS depressants, and not to use such drugs unless supervised by a health care provider.

Important Administration Instructions

Instruct patients how to properly take OXYCODONE HCl EXTENDED-RELEASE TABLETS, including the following:

OXYCODONE HCl EXTENDED-RELEASE TABLETS are designed to work properly only if swallowed intact.Taking cut, broken, chewed, crushed, or dissolved OXYCODONE HCl EXTENDED-RELEASE TABLETS can result in a fatal overdose.
OXYCODONE HCl EXTENDED-RELEASE TABLETS should be taken one tablet at a time.
Do not pre-soak, lick or otherwise wet the tablet prior to placing in the mouth.
Take each tablet with enough water to ensure complete swallowing immediately after placing in the mouth.

Hypotension

Inform patients that OXYCODONE HCl EXTENDED-RELEASE TABLETS may cause orthostatic hypotension and syncope. Instruct patients how to recognize symptoms of low blood pressure and how to reduce the risk of serious consequences should hypotension occur (e.g., sit or lie down, carefully rise from a sitting or lying position).

Driving or Operating Heavy Machinery

Inform patients that OXYCODONE HCl EXTENDED-RELEASE TABLETS may impair the ability to perform potentially hazardous activities such as driving a car or operating heavy machinery. Advise patients not to perform such tasks until they know how they will react to the medication.

Constipation

Advise patients of the potential for severe constipation, including management instructions and when to seek medical attention.

Anaphylaxis

Inform patients that anaphylaxis has been reported with ingredients contained in OXYCODONE HCl EXTENDED-RELEASE TABLETS. Advise patients how to recognize such a reaction and when to seek medical attention.

Pregnancy

Advise female patients that OXYCODONE HCl EXTENDED-RELEASE TABLETS can cause fetal harm and to inform the prescriber if they are pregnant or plan to become pregnant.

Disposal of Unused Oxycodone Hydrochloride Extended-release Tablets

Advise patients to flush the unused tablets down the toilet when OXYCODONE HCl EXTENDED-RELEASE TABLETS are no longer needed.

SPL UNCLASSIFIED SECTION

Healthcare professionals can telephone Impax Laboratories, Inc. at 1-800-934-6729 for information on this product.

Manufactured by:
Purdue Pharmaceuticals L.P.
Wilson, NC 27893

Distributed by :
Impax Generics
Hayward, CA 94544

U.S. Patent Numbers 6,488,963; 7,129,248; 7,674,799; 7,674,800; 7,683,072; 8,114,383; 8,309,060; 8,337,888; 8,808,741; 8,821,929; 8,894,987; 8,894,988; 9,060,976; and 9,073,933.

303911-0A
Rev. 08/2015

MEDICATION GUIDE

OXYCODONE Hydrochloride (ox-e-KO-don hye-droe-KLOR-ide) Extended-release Tablets, for oral use, CII

OXYCODONE HCl EXTENDED-RELEASE TABLETS are:

A strong prescription pain medicine that contains an opioid (narcotic) that is used to manage pain severe enough to require daily around-the-clock, long-term treatment with an opioid, when other pain treatments such as non-opioid pain medicines or immediate-release opioid medicines do not treat your pain well enough or you cannot tolerate them.
A long-acting (extended-release) opioid pain medicine that can put you at risk for overdose and death. Even if you take your dose correctly as prescribed you are at risk for opioid addiction, abuse, and misuse that can lead to death.
Not for use to treat pain that is not around-the-clock.
Not for use in children less than 11 years of age and who are not already using opioid pain medicines regularly to manage pain severe enough to require daily around-the-clock long-term treatment of pain with an opioid.

Important information about OXYCODONE HCl EXTENDED-RELEASE TABLETS:

Get emergency help right away if you take too much OXYCODONE HCl EXTENDED-RELEASE TABLETS (overdose). When you first start taking OXYCODONE HCl EXTENDED-RELEASE TABLETS, when your dose is changed, or if you take too much (overdose), serious or life-threatening breathing problems that can lead to death may occur.
Never give anyone else your OXYCODONE HCl EXTENDED-RELEASE TABLETS. They could die from taking it. Store OXYCODONE HCl EXTENDED-RELEASE TABLETS away from children and in a safe place to prevent stealing or abuse. Selling or giving away OXYCODONE HCl EXTENDED-RELEASE TABLETS is against the law.

Do not take OXYCODONE HCl EXTENDED-RELEASE TABLETS if you have:

severe asthma, trouble breathing, or other lung problems.
a bowel blockage or have narrowing of the stomach or intestines.

Before taking OXYCODONE HCl EXTENDED-RELEASE TABLETS, tell your healthcare provider if you have a history of:

head injury, seizures
liver, kidney, thyroid problems
problems urinating
pancreas or gallbladder problems
abuse of street or prescription drugs, alcohol addiction, or mental health problems.

Tell your healthcare provider if you are:

pregnant or planning to become pregnant.Prolonged use of OXYCODONE HCl EXTENDED-RELEASE TABLETS during pregnancy can cause withdrawal symptoms in your newborn baby that could be life-threatening if not recognized and treated.
breastfeeding. OXYCODONE HCl EXTENDED-RELEASE TABLETS pass into breast milk and may harm your baby.
taking prescription or over-the-counter medicines, vitamins, or herbal supplements. Taking OXYCODONE HCl EXTENDED-RELEASE TABLETS with certain other medicines can cause serious side effects that could lead to death.

When taking oxycodone hydrochloride extended-release tablets:

Do not change your dose. Take OXYCODONE HCL EXTENDED-RELEASE TABLETS exactly as prescribed by your healthcare provider.
Take your prescribed dose every 12 hours at the same time every day. Do not take more than your prescribed dose in 12 hours. If you miss a dose, take your next dose at your usual time.
Swallow OXYCODONE HCL EXTENDED-RELEASE TABLETS whole. Do not cut, break, chew, crush, dissolve, snort, or inject OXYCODONE HCL EXTENDED-RELEASE TABLETS because this may cause you to overdose and die.
OXYCODONE HCL EXTENDED-RELEASE TABLETS should be taken 1 tablet at a time. Do not pre-soak, lick, or wet the tablet before placing in your mouth to avoid choking on the tablet.
Call your healthcare provider if the dose you are taking does not control your pain.
Do not stop taking OXYCODONE HCL EXTENDED-RELEASE TABLETS without talking to your healthcare provider.
After you stop taking OXYCODONE HCL EXTENDED-RELEASE TABLETS, flush any unused tablets down the toilet.

While taking OXYCODONE HCL EXTENDED-RELEASE TABLETS DO NOT:

Drive or operate heavy machinery, until you know how OXYCODONE HCL EXTENDED-RELEASE TABLETS affect you. OXYCODONE HCL EXTENDED-RELEASE TABLETS can make you sleepy, dizzy, or lightheaded.
Drink alcohol, or use prescription or over-the-counter medicines that contain alcohol. Using products containing alcohol during treatment with OXYCODONE HCL EXTENDED-RELEASE TABLETS may cause you to overdose and die.

The possible side effects of OXYCODONE HCL EXTENDED-RELEASE TABLETS are:

constipation, nausea, sleepiness, vomiting, tiredness, headache, dizziness, abdominal pain. Call your healthcare provider if you have any of these symptoms and they are severe.

Get emergency medical help if you have:

trouble breathing, shortness of breath, fast heartbeat, chest pain, swelling of your face, tongue or throat, extreme drowsiness, light-headedness when changing positions, or you are feeling faint.

These are not all the possible side effects of OXYCODONE HCL EXTENDED-RELEASE TABLETS. Call your doctor for medical advice about side effects. You may report side effects to FDA at 1-800-FDA-1088. For more information go to dailymed.nlm.nih.gov

This Medication Guide has been approved by the U.S. Food and Drug Administration.

Dist By: Impax Laboratories, Inc., Hayward, CA 94544

Rev. 08/2015
303911-0A